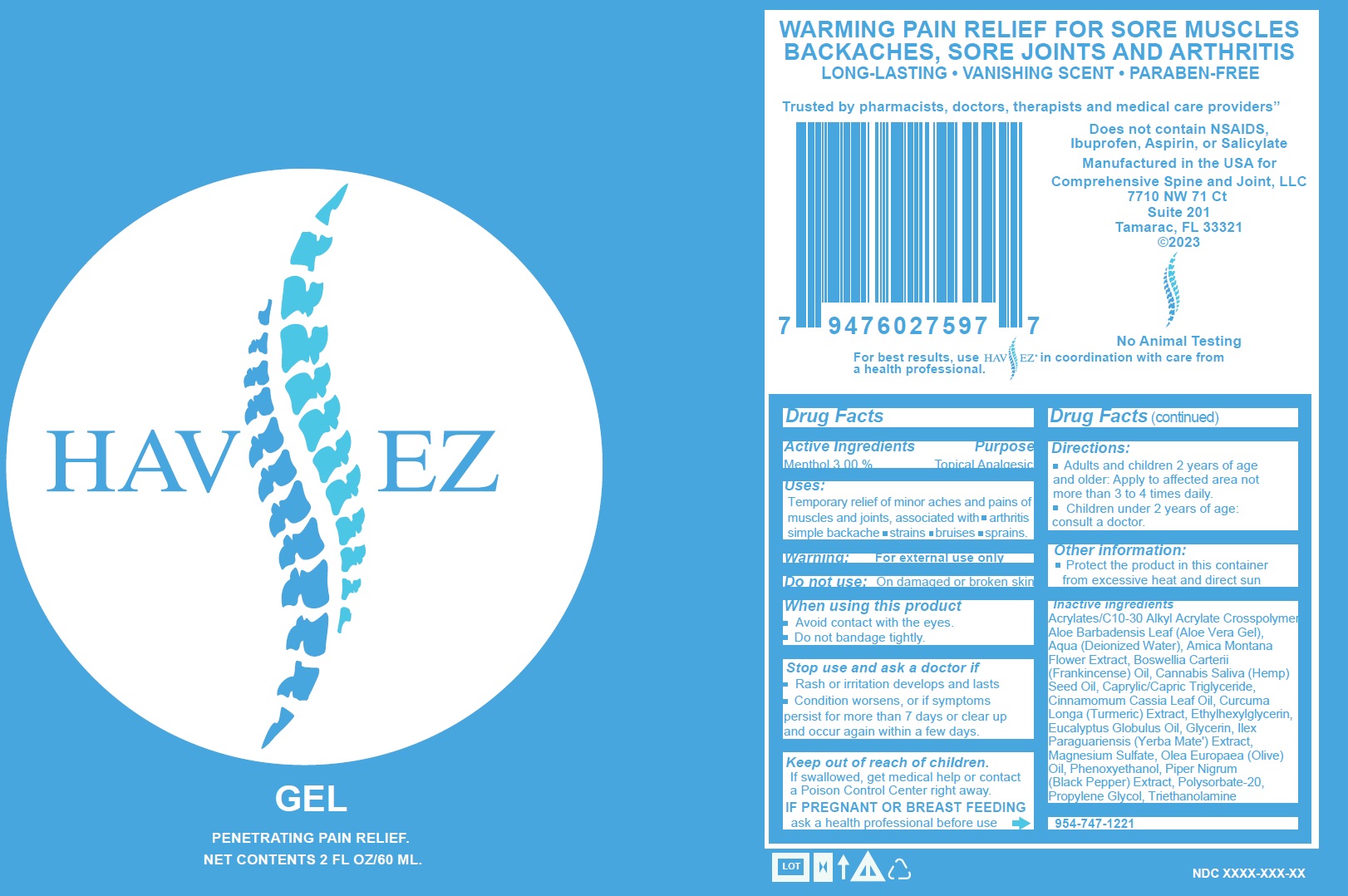 DRUG LABEL: HAV EZ Penetrating Pain Relief
NDC: 84093-442 | Form: GEL
Manufacturer: PALM ORTHOPEDICS & INTERVENTIONAL PAIN LLC
Category: otc | Type: HUMAN OTC DRUG LABEL
Date: 20240201

ACTIVE INGREDIENTS: MENTHOL 30 mg/1 mL
INACTIVE INGREDIENTS: ALOE VERA LEAF; WATER; FRANKINCENSE; HEMP; MEDIUM-CHAIN TRIGLYCERIDES; CHINESE CINNAMON LEAF OIL; TURMERIC; ETHYLHEXYLGLYCERIN; EUCALYPTUS OIL; GLYCERIN; MAGNESIUM SULFATE, UNSPECIFIED FORM; GREEN OLIVE; PHENOXYETHANOL; BLACK PEPPER; POLYSORBATE 20; PROPYLENE GLYCOL; TROLAMINE

HAV EZ Penetrating Pain Relief Gel

Active Ingredients

Menthol 3.00 %

Purpose

Topical Analgesic

Uses:

Temporary relief of minor aches and pains of muscles and joints, associated with • arthritis simple backache • strains • bruises • sprains.

Warning:

For external use only

Do not use:

On damaged or broken skin

When using this product

- Avoid contact with the eyes.
- Do not bandage tightly.

Stop use and ask a doctor if

- Rash or irritation develops and lasts
- Condition worsens, or if symptoms persist for more than 7 days or clear up and occur again within a few days.

Keep out of reach of children.

If swallowed, get medical help or contact a Poison Control Center right away.

IF PREGNANT OR BREAST FEEDING

ask a health professional before use

Directions:

- Adults and children 2 years of age and older: Apply to affected area not more than 3 to 4 times daily.
- Children under 2 years of age: consult a doctor.

Other information:

- Protect the product in this container from excessive heat and direct sun

Inactive ingredients

Acrylates/C10-30 Alkyl Acrylate Crosspolymer, Aloe Barbadensis Leaf (Aloe Vera Gel), Aqua (Deionized Water), Amica Montana Flower Extract, Boswellia Carterii (Frankincense) Oil, Cannabis Saliva (Hemp) Seed Oil, Caprylic/Capric Triglyceride, Cinnamomum Cassia Leaf Oil, Curcuma Longa (Turmeric) Extract, Ethylhexylglycerin, Eucalyptus Globulus Oil, Glycerin, Ilex Paraguariensis (Yerba Mate') Extract, Magnesium Sulfate, Olea Europaea (Olive) Oil, Phenoxyethanol, Piper Nigrum (Black Pepper) Extract, Polysorbate-20, Propylene Glycol, Triethanolamine

QUESTIONS

954-747-1221